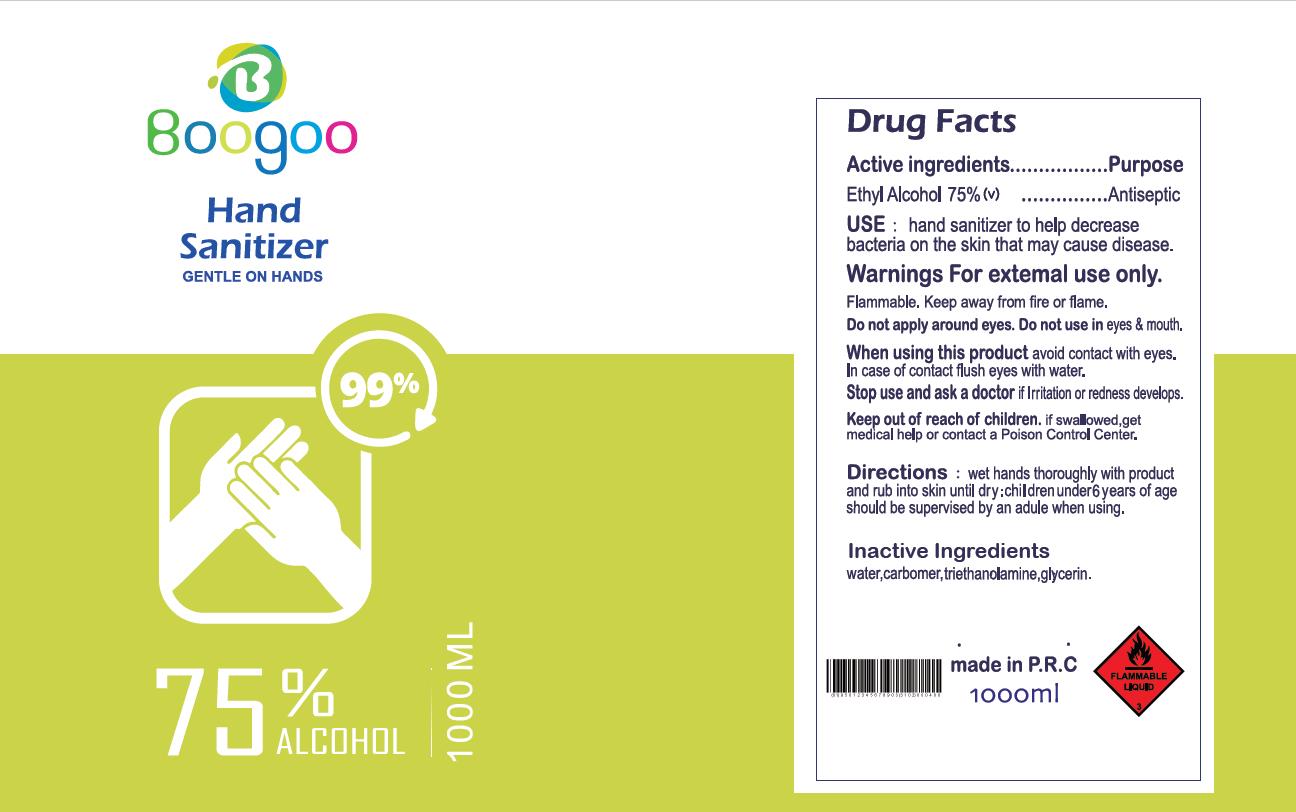 DRUG LABEL: Boogoo Hand Sanitizer
NDC: 79793-001 | Form: GEL
Manufacturer: Ningbo Wingspan Commodity Co., Ltd.
Category: otc | Type: HUMAN OTC DRUG LABEL
Date: 20200724

ACTIVE INGREDIENTS: ALCOHOL 75 mL/100 mL
INACTIVE INGREDIENTS: CARBOMER HOMOPOLYMER, UNSPECIFIED TYPE; TROLAMINE; GLYCERIN; WATER

Active ingredients

Ethyl Alcohol 75%(v)

Purpose

Antiseptic

Use

hand sanitizer to help decrease bacteria on the skin that may cause disease.

Warnings

For external use only.

Flammable, keep away from fire or flame.

Do not use

Do not apply around eyes. Do not use in eyes & mouth.

When using this product avoid contact with eyes. In case of contact flush eyes with water.

Stop use and ask a doctor if irritation or redness develops.

Keep out of reach of children

if swallowed, get medical help or contact a Poison Control Center.

Directions

wet hands thoroughly with product and rub into skin until dry. Children under 6 years of age should be supervised by an adult when using.

Inactive Ingredient

water

carbomer

triethanolamine,

glycerin